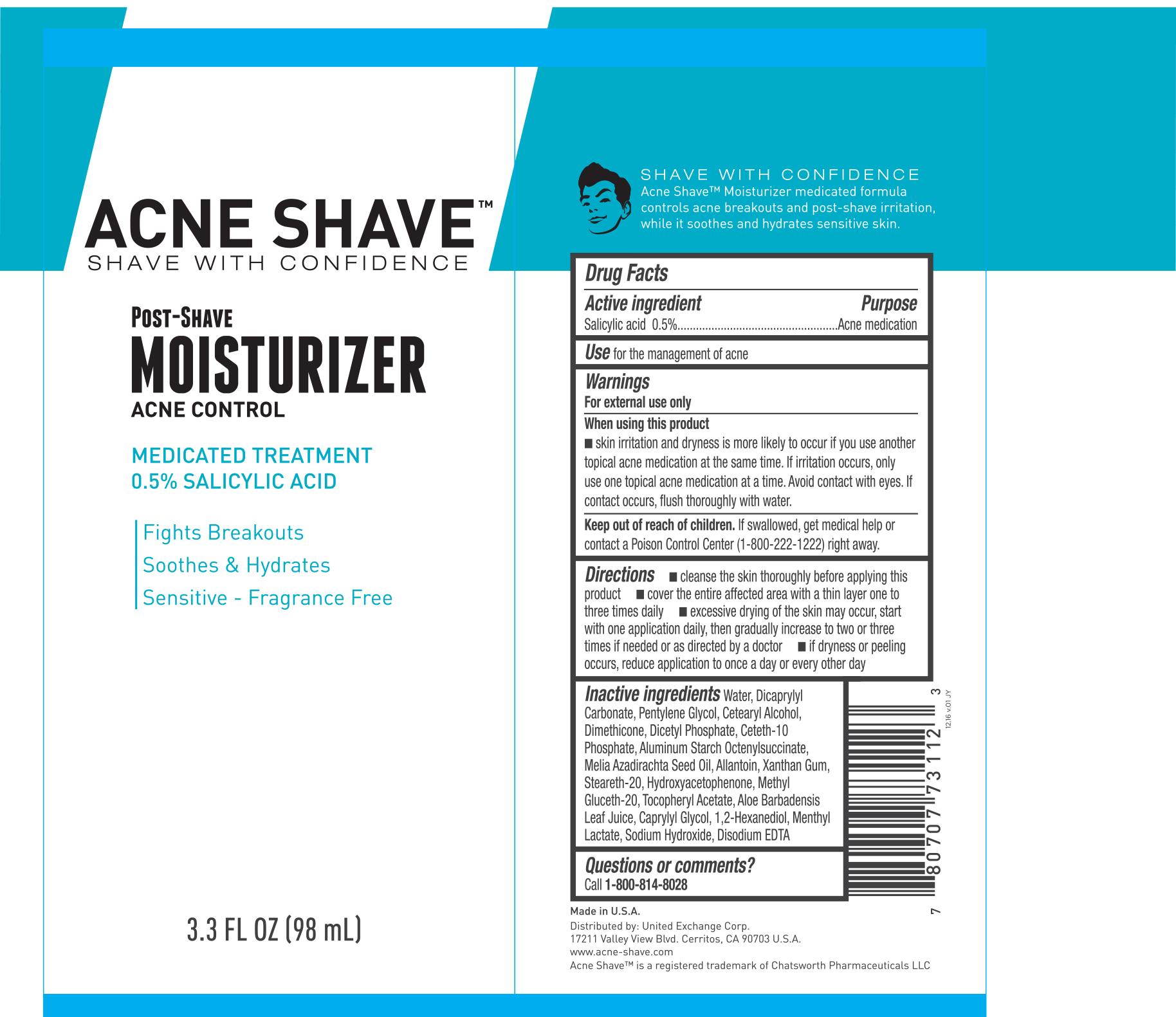 DRUG LABEL: Acne Shave Moisturizer
NDC: 65923-112 | Form: CREAM
Manufacturer: United Exchange Corp.
Category: otc | Type: HUMAN OTC DRUG LABEL
Date: 20170725

ACTIVE INGREDIENTS: SALICYLIC ACID 0.5 mg/1 mL
INACTIVE INGREDIENTS: WATER; DIMETHICONE; ALUMINUM STARCH OCTENYLSUCCINATE; XANTHAN GUM; HYDROXYACETOPHENONE; METHYL GLUCETH-20; .ALPHA.-TOCOPHEROL ACETATE; DICAPRYLYL CARBONATE; PENTYLENE GLYCOL; CETOSTEARYL ALCOHOL; DIHEXADECYL PHOSPHATE; CETETH-10 PHOSPHATE; AZADIRACHTA INDICA SEED OIL; ALLANTOIN; STEARETH-20; CAPRYLYL GLYCOL; 1,2-HEXANEDIOL; METHYL LACTATE, DL-; SODIUM HYDROXIDE; EDETATE DISODIUM; ALOE VERA LEAF

Acne Shave Moisturizer 3.3 oz 73112 (2017)

Active ingredient Purpose

Salicylic acid 0.5%.................................Acne medication

Use

for the management of acne

Warnings

For external use only

When using this product

- skin irritation and dryness is more likely to occur if you use another topical acne medication at the same time. If irritation occurs, only use one topical acne medication at a time. Avoid contact with eyes. If contact occurs, flush thoroughly with water.

Keep out of reach of children. If swallowed, get medical help or contact a Poison Control Center (1-800-222-1222) right away.

Directions

- cleanse the skin thoroughly before applying this product
- cover the entire affected area with a thin layer one to three times daily
- excessive drying of the skin may occur, start with one application daily, then gradually increase to two or three times if needed or as directed by a doctor
- if dryness or peeling occurs, reduce application to once a day or every other day

Inactive ingredients

Water, Dicaprylyl Carbonate, Pentylene Glycol, Cetearyl Alcohol, Dimethicone, Dicetyl Phosphate, Ceteth-10 Phosphate, Aluminum Starch Octenylsuccinate, Melia Azardirachta Seed Oil, Allantoin, Xanthan Gum, Steareth-20, Hydroxyacetophenone, Methyl Gluceth-20, Tocopheryl Acetate, Aloe Barbadensis Leaf Juice, Caprylyl Glycol, 1,2-Hexanediol, Methyl Lactate, Sodium Hydroxide, Disodium EDTA

DOSAGE AND ADMINISTRATION

Distributed by:

17211 Valley View

Cerritos, CA 90703 USA